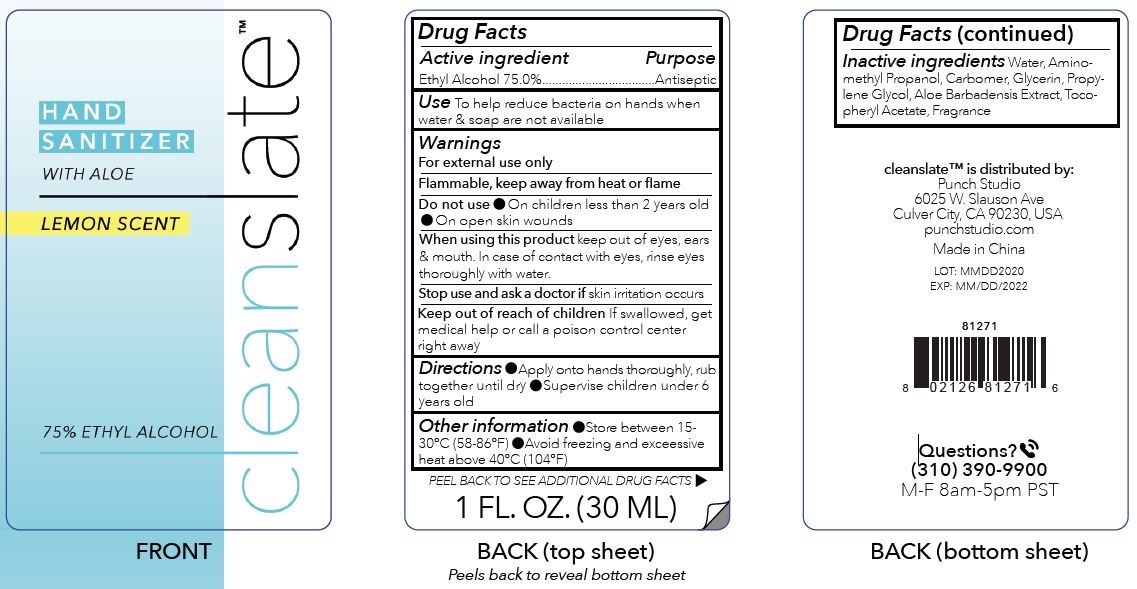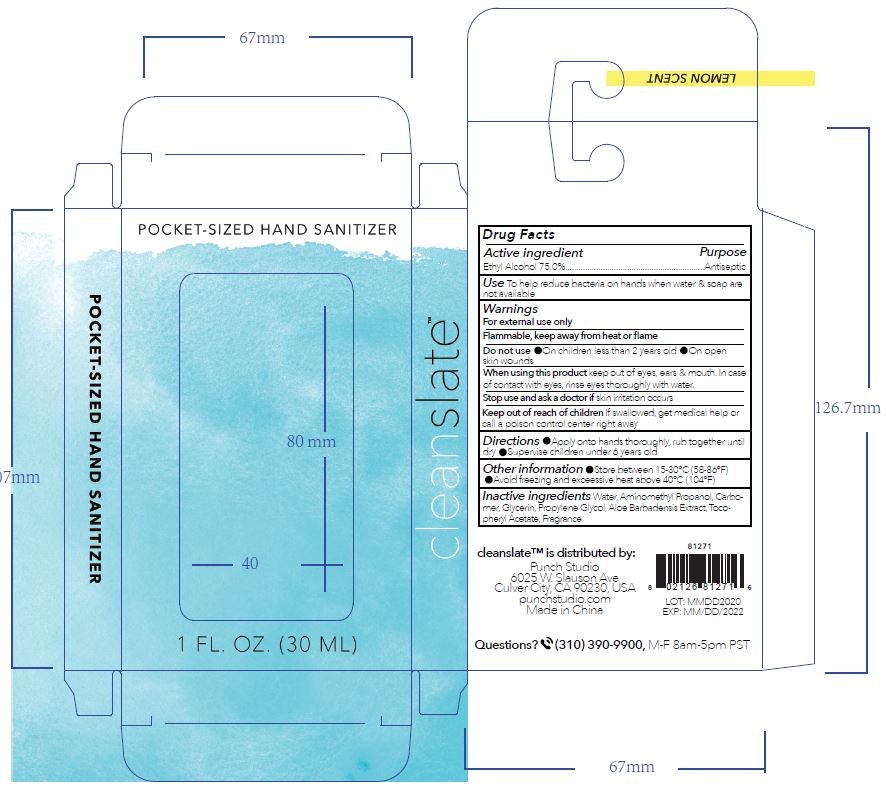 DRUG LABEL: Cleanslate
NDC: 75601-1004 | Form: LIQUID
Manufacturer: Punch Studio, LLC
Category: otc | Type: HUMAN OTC DRUG LABEL
Date: 20220112

ACTIVE INGREDIENTS: ALCOHOL 75 mL/100 mL
INACTIVE INGREDIENTS: GLYCERIN; AMINOMETHYLPROPANOL; WATER; ALOE VERA LEAF; CARBOMER HOMOPOLYMER, UNSPECIFIED TYPE; PROPYLENE GLYCOL; ALPHA-TOCOPHEROL ACETATE

Hand Sanitizer

Active Ingredient(s)

Ethyl Alcohol 75% Purpose: Antiseptic

Purpose

Antiseptic

Use

To help reduce bacteria on hands when water & soap are not available

Warnings

For external use only

Flammable. Keep away from heat or flame

Do not use

- On children less than 2 years old
- On open skin wounds

When using this product keep out of eyes, ears, and mouth. In case of contact with eyes, rinse eyes thoroughly with water.

Stop use and ask a doctor if skin irritation occurs.

Keep out of reach of children If swallowed, get medical help or contact a poison control center right away

Directions

- Apply onto hands thoroughly, rub together until dry
- Supervise children under 6 years old

Other information

- Store between 15-30°C (59-86°F)
- Avoid freezing and excessive heat above 40°C (104°F)

Inactive ingredients

Water, Aminomethyl Propanol, Carbomer, Glycerin, Propylene Glycol, Aloe Barbadensis Extract, Tocopheryl Acetate, Fragrance

Package Label - Principal Display Panel

30 mL NDC: 75601-1271-1 30 mL NDC: 75601-1271-2